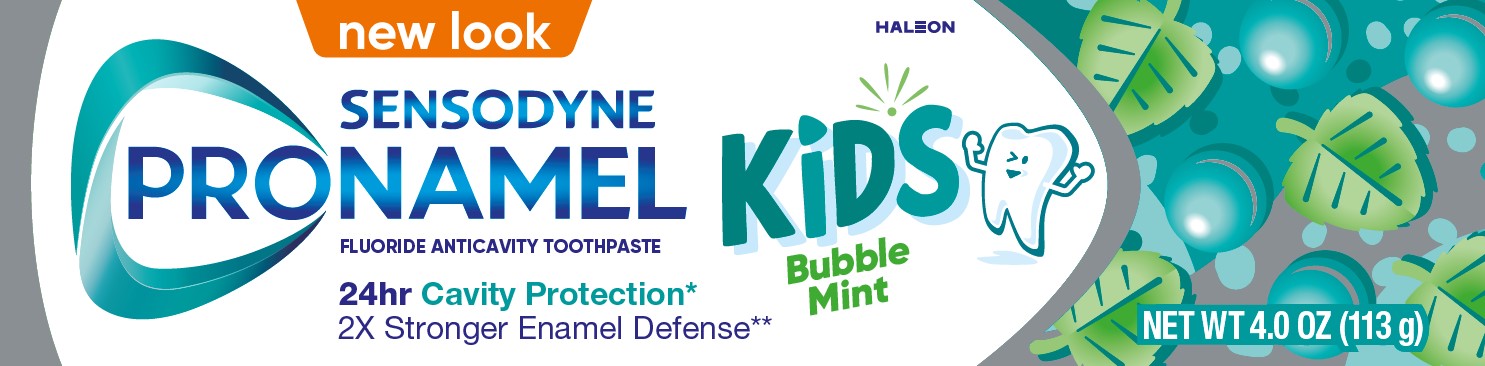 DRUG LABEL: Sensodyne Pronamel

NDC: 0135-0818 | Form: PASTE, DENTIFRICE
Manufacturer: Haleon US Holdings LLC
Category: otc | Type: HUMAN OTC DRUG LABEL
Date: 20251215

ACTIVE INGREDIENTS: SODIUM FLUORIDE 1.1 mg/1 g
INACTIVE INGREDIENTS: WATER; SORBITOL; HYDRATED SILICA; GLYCERIN; POLYETHYLENE GLYCOL 400; COCAMIDOPROPYL BETAINE; XANTHAN GUM; SACCHARIN SODIUM; SODIUM HYDROXIDE; FD&C BLUE NO. 1

Drug Facts

Active ingredient

Sodium fluoride 0.245% (0.15% w/v fluoride ion)

Purpose

Anticavity

Use

- aids in the prevention of dental cavities.

Warnings

Keep out of reach of children under 6 years of age.

If more than used for brushing is accidentally swallowed, get medical help or contact a Poison Control Center right away.

Directions

- adults and children 2 years of age and older:
  - brush teeth thoroughly, preferably after each meal or at least twice a day, and not more than 3 times a day, or as directed by a dentist or doctor. Minimize swallowing. Spit out after brushing.
  - to minimize swallowing for children under 6 years of age, use a pea-sized amount and supervise brushing and rinsing until good habits are established.
- children under 2 years of age:Consult a dentist or doctor.

Other information

- do not store above 25°C (77°F)

Inactive ingredients

water, sorbitol, hydrated silica, glycerin, PEG-8, cocamidopropyl betaine, xanthan gum, flavor, sodium saccharin, sodium hydroxide, blue 1

Questions or comments?

1-866-844-2797

Additional Information

ALWAYS FOLLOW THE LABEL

SENSODYNE PRONAMEL

Bubble Mint KiDS

#1 DENTIST RECOMMENDED TOOTHPASTE FOR PROTECTING AND STRENGTHENING ENAMEL

Adults | Kids

Kids enamel is 50% thinner

Kids enamel is 50% thinner vs an Adults

This makes kids’ teeth more vulnerable to everyday sugar & dietary acids like fruit and juices.

24hr Cavity Protection*

2x Stronger Enamel Defense**

Pronamel Kidsstrengthens and protects developing enamel. Strong enamel is the best defense against cavities and enamel wear.

Pronamel for Kidsprovides:

24 hour Cavity Protection*

2x Stronger Enamel Defense**

Natural Flavors

Gluten Free

Vegan Friendly***

Sugar, SLS & Paraben Free

*Follow a healthy diet and brush twice daily. (Level of protection may decrease between brushing.) **Protection from sugar acids vs your mouth’s natural defenses. ***Contains no animal products and animal derived products.

Principal Display Panel

new look

SENSODYNE PRONAMEL

KiDS Bubble Mint

FLUORIDE ANTICAVITY TOOTHPASTE

24hr Cavity Protection*

2X Stronger Enamel Defense**

NET WT 4.0 OZ (113 g)